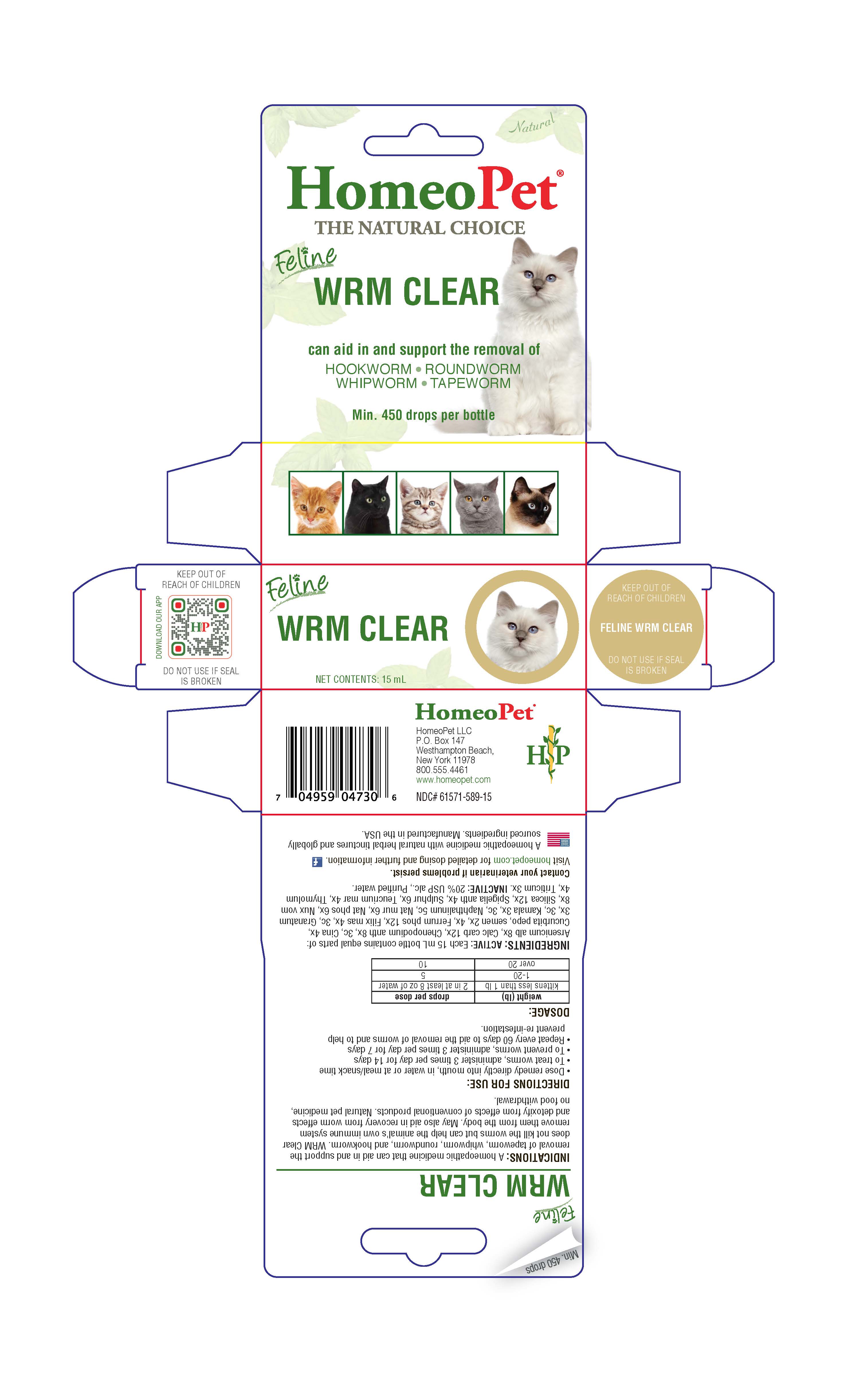 DRUG LABEL: Wrm Clear
NDC: 61571-589 | Form: LIQUID
Manufacturer: HomeoPet, LLC
Category: homeopathic | Type: OTC ANIMAL DRUG LABEL
Date: 20221130

ACTIVE INGREDIENTS: ARSENIC TRIOXIDE 8 [hp_X]/15 mL; OYSTER SHELL CALCIUM CARBONATE, CRUDE 12 [hp_X]/15 mL; CHENOPODIUM AMBROSIOIDES  8 [hp_X]/15 mL; ARTEMISIA CINA FLOWER 4 [hp_X]/15 mL; PUMPKIN SEED 2 [hp_X]/15 mL; FERRUM PHOSPHORICUM 12 [hp_X]/15 mL; DRYOPTERIS FILIX-MAS ROOT 4 [hp_X]/15 mL; PUNICA GRANATUM ROOT BARK 3 [hp_X]/15 mL; KAMALA 3 [hp_X]/15 mL; SODIUM CHLORIDE 6 [hp_X]/15 mL; SODIUM PHOSPHATE, DIBASIC, HEPTAHYDRATE 6 [hp_X]/15 mL; NAPHTHALENE 5 [hp_C]/15 mL; STRYCHNOS NUX-VOMICA SEED 8 [hp_X]/15 mL; SILICON DIOXIDE 12 [hp_X]/15 mL; SPIGELIA ANTHELMIA 4 [hp_X]/15 mL; SULFUR 6 [hp_X]/15 mL; TEUCRIUM MARUM 4 [hp_X]/15 mL; THYMOL  4 [hp_X]/15 mL; ELYMUS REPENS TOP 3 [hp_X]/15 mL
INACTIVE INGREDIENTS: ALCOHOL; WATER

FELINE WRM CLEAR

Feline Wrm Clear

Can aid in and support the removal of

HOOKWORM-ROUNDWORM-WHIPWORM-TAPEWORM

Directions for Use

- Dose remedy directly into mouth, in water or at meal/snack time
- To treat worms, administer 3 times per day for 14 days
- To prevent worms, administer 3 times per day for 7 days
- Repeat every 60 days to remove or prevent worms

Dosage:

weight (lb) | drops per dose
kittens less than 1 lb | 2 in at least 8 oz of water
1-20 | 5
over 20 | 10

ASK DOCTOR

Contact Veterinarian if problems persist.

Visit homeopet.com for detailed dosing and further information.

Ingredients HPUS: Active:

Arsenicum alb 8x, Calc carb 12x, Chenopodium anth 8x, 3c, Cina 4x, Cucurbita pepo, semen 2x, 4x, Ferrum phos 12x, Filix mas 4x, 3c, Granatum 3x, 3c, Kamala 3x, 3c, Naphthalinum 5c, Nat mur 6x, Nat phos 6x, Nux vom 8x, Silicea 12x, Spigelia anth 4x, Sulphur 6x, Teucrium mar 4x, Thymolum 4x, Triticum 3x.

Inactive Ingredients

USP Alcohol, Purified water

Indications:

A natural homeopathic remedy that can aid in and support the removal of tapeworm, whipworm, roundworm and hookworm. WRM Clear does not kill the worms but can help the animal's own immune system remove them from the body. may also aid in recovery from worm effects and detoxify from effects of convenational products. 100% natural, no chemicals added, no food withdrawal.

PACKAGE LABEL

Add image transcription here...